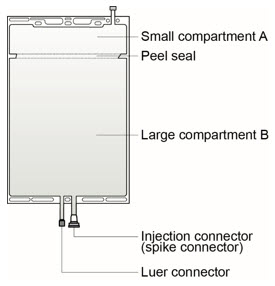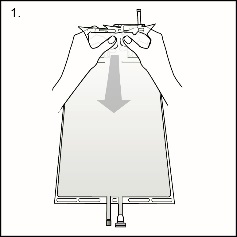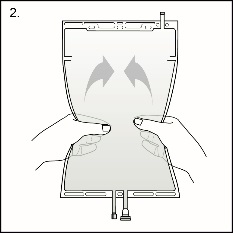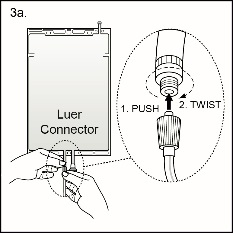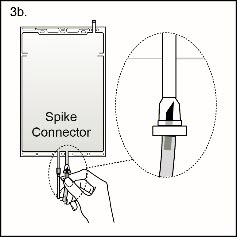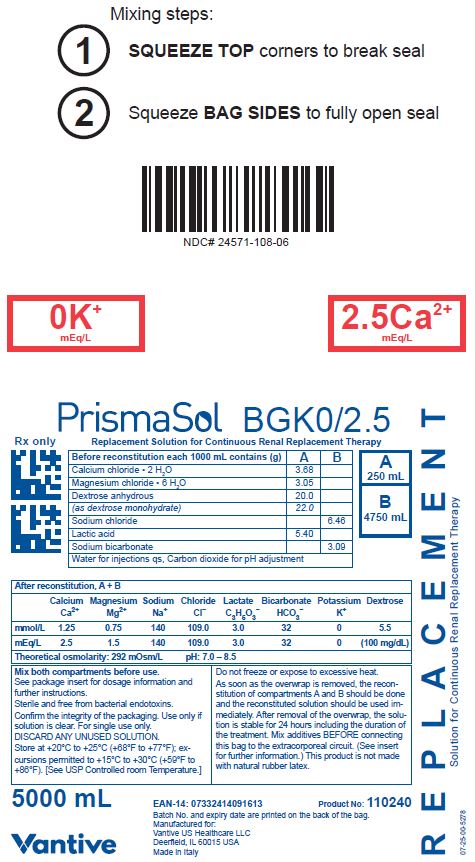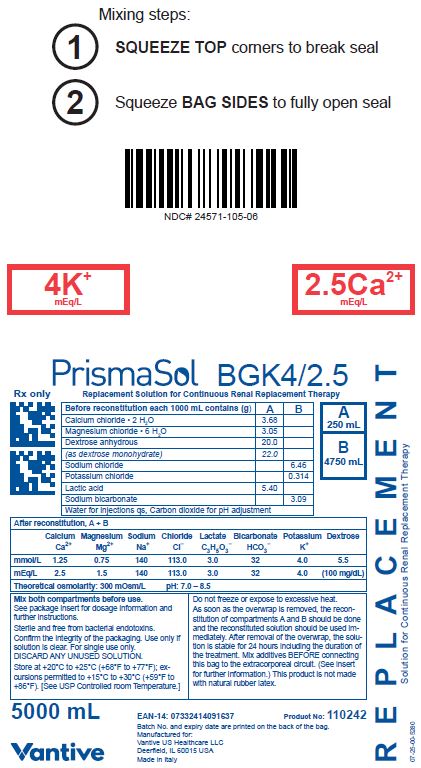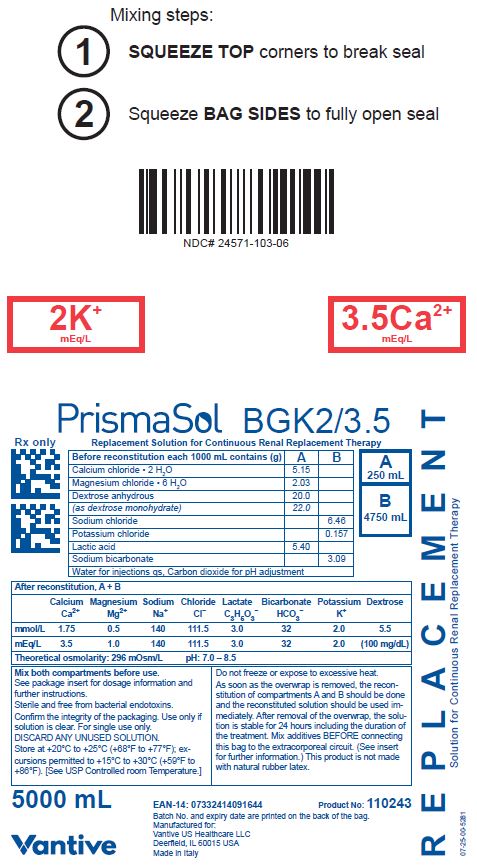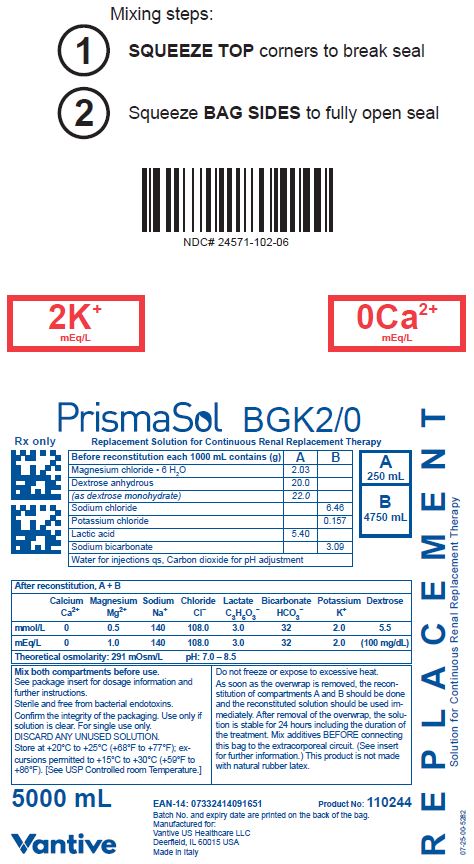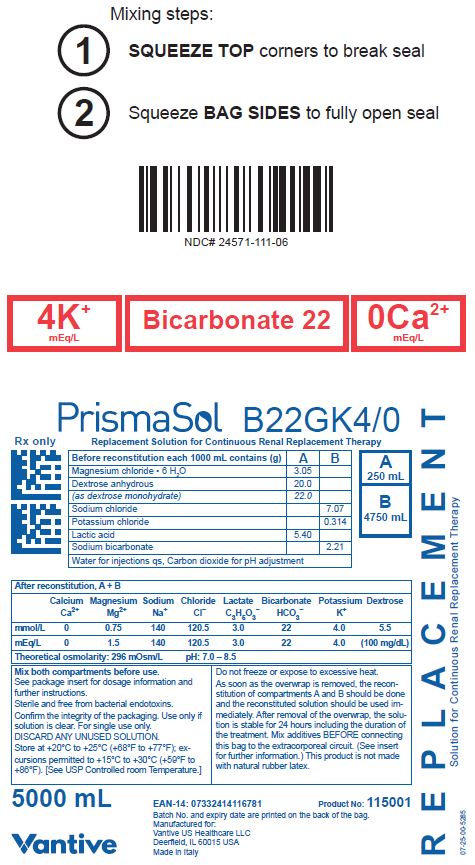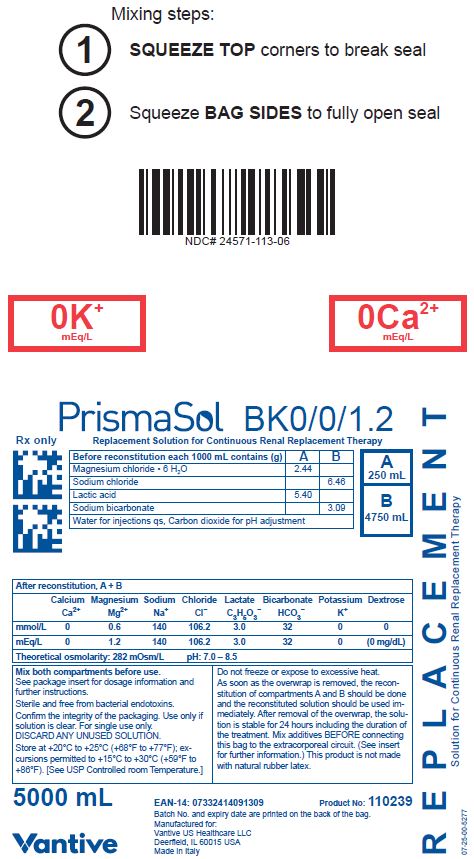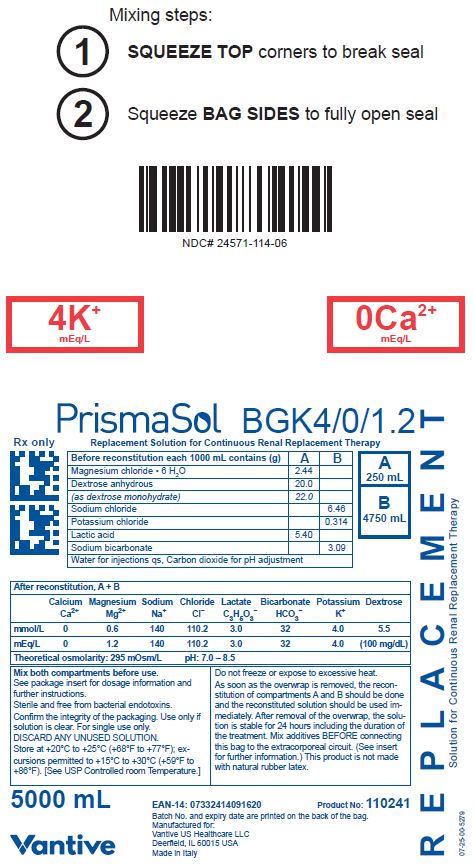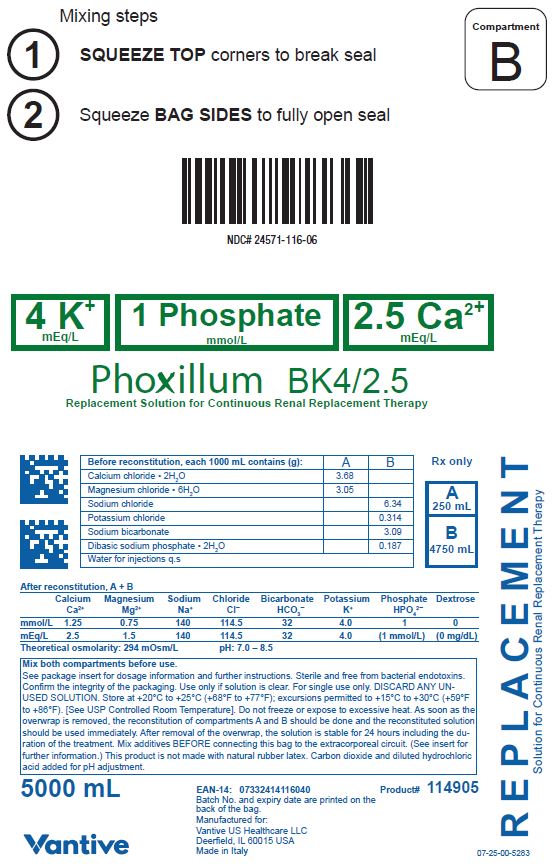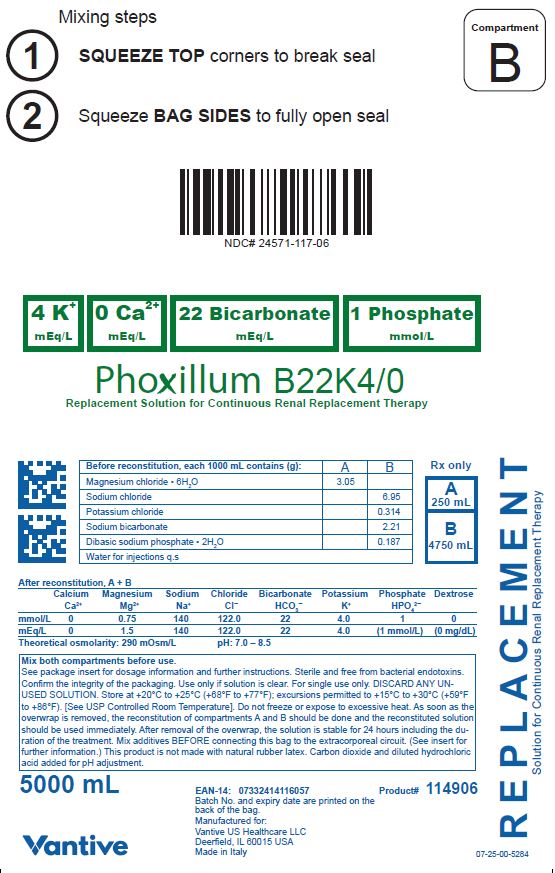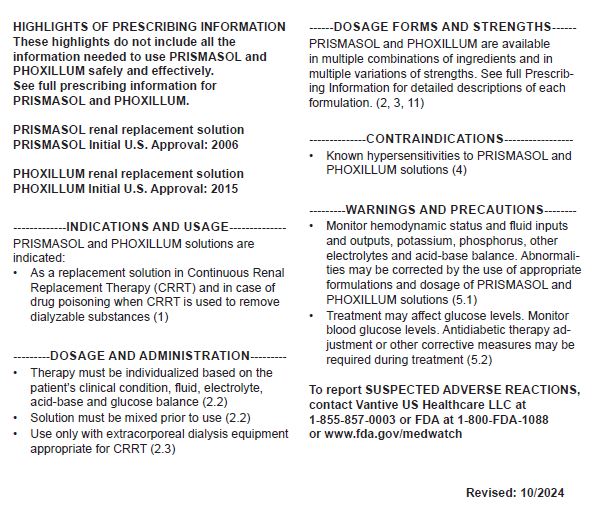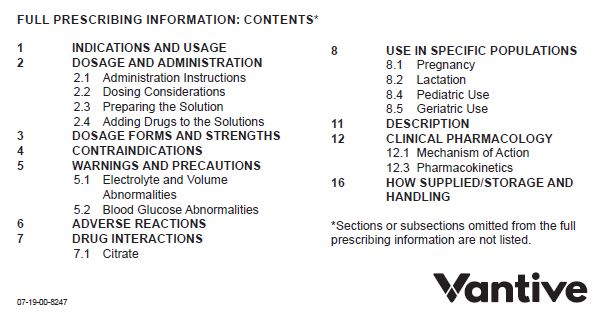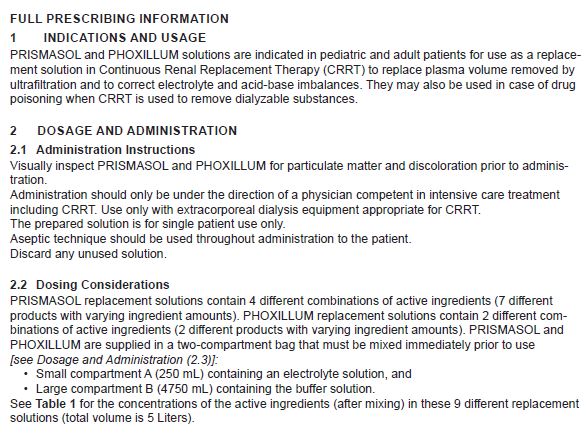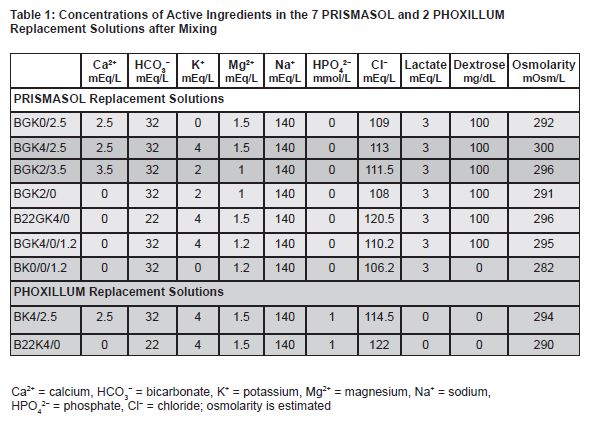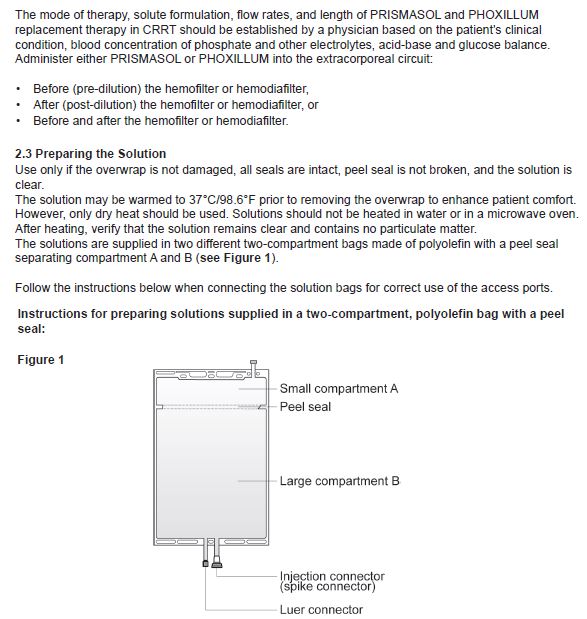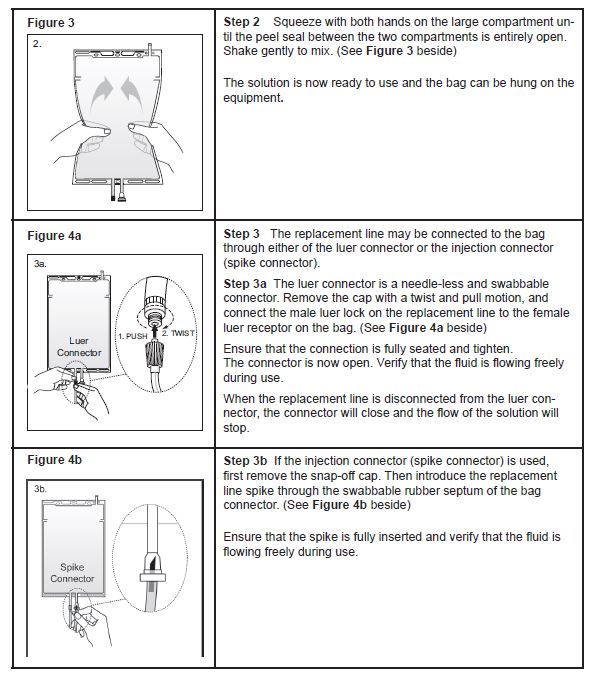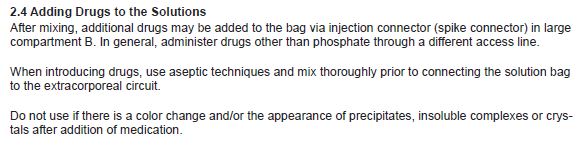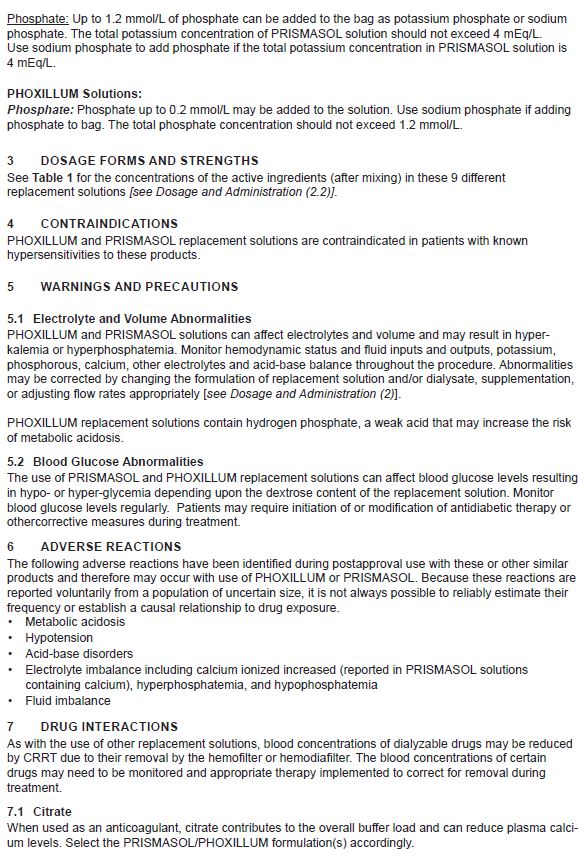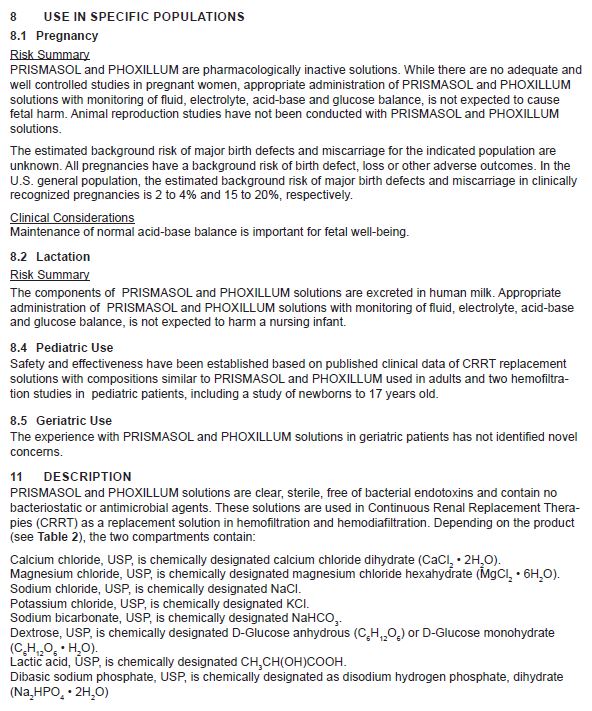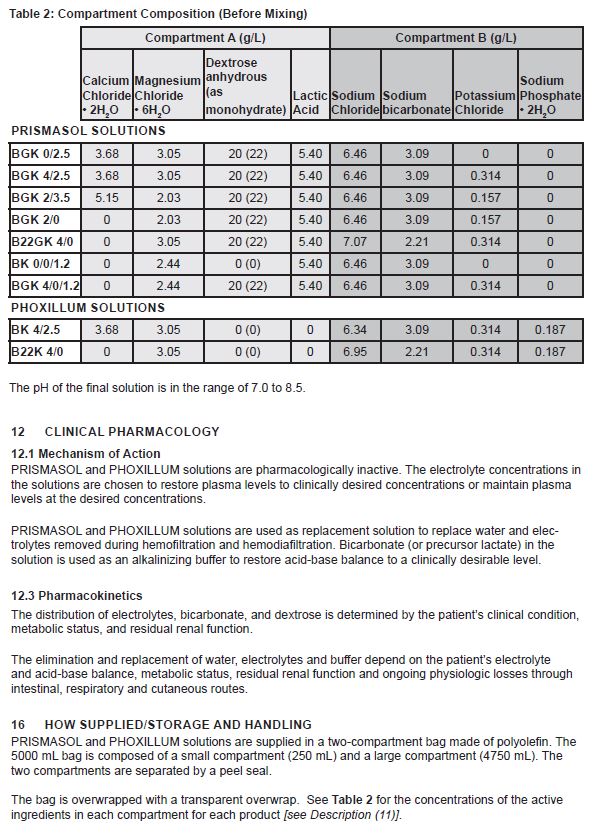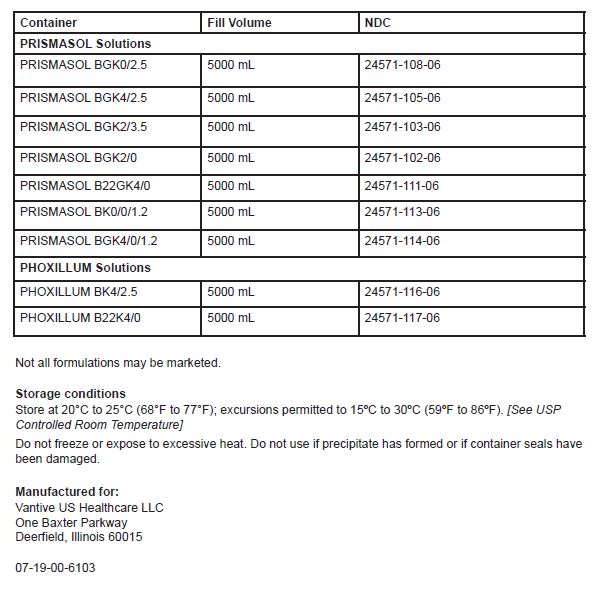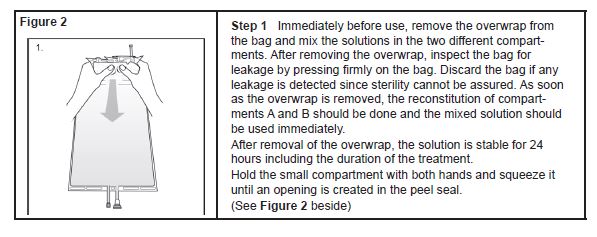 DRUG LABEL: PRISMASOL

NDC: 24571-108 | Form: INJECTION
Manufacturer: Vantive US Healthcare LLC
Category: prescription | Type: HUMAN PRESCRIPTION DRUG LABEL
Date: 20250313

ACTIVE INGREDIENTS: CALCIUM CHLORIDE 3.68 g/1 L; MAGNESIUM CHLORIDE 3.05 g/1 L; ANHYDROUS DEXTROSE 20 g/1 L; LACTIC ACID 5.4 g/1 L; SODIUM CHLORIDE 6.46 g/1 L; SODIUM BICARBONATE 3.09 g/1 L
INACTIVE INGREDIENTS: WATER; CARBON DIOXIDE

HIGHLIGHTS OF PRESCRIBING INFORMATION

These highlights do not include all the information needed to use PRISMASOL and PHOXILLUM safely and effectively. See full prescribing information for PRISMASOL and PHOXILLUM.
PRISMASOL renal replacement solution
PRISMASOL Initial U.S. Approval: 2006
PHOXILLUM renal replacement solution
PHOXILLUM Initial U.S. Approval: 2015

1 INDICATIONS AND USAGE

PRISMASOL and PHOXILLUM solutions are indicated:

- As a replacement solution in Continuous Renal Replacement Therapy (CRRT) and in case of drug poisoning when CRRT is used to remove dialyzable substances (1)

2 DOSAGE AND ADMINISTRATION

- Therapy must be individualized based on the patient's clinical condition, fluid, electrolyte, acid-base and glucose balance (2.2)
- Solution must be mixed prior to use (2.2)
- Use only with extracorporeal dialysis equipment appropriate for CRRT (2.3)

3 DOSAGE FORMS AND STRENGTHS

PRISMASOL and PHOXILLUM are available in multiple combinations of ingredients and in multiple variations of strengths. See full Prescribing Information for detailed descriptions of each formulation. (2, 3, 11)

4 CONTRAINDICATIONS

Known hypersensitivities to PRISMASOL and PHOXILLUM solutions (4)

5 WARNINGS AND PRECAUTIONS

- Monitor hemodynamic status and fluid inputs and outputs, potassium, phosphorus, other electrolytes and acid-base balance. Abnormalities may be corrected by the use of appropriate formulations and dosage of PRISMASOL and PHOXILLUM solutions (5.1)
- Treatment may affect glucose levels. Monitor blood glucose levels.
- Antidiabetic therapy adjustment or other corrective measures may be required during treatment (5.2)

To report SUSPECTED ADVERSE REACTIONS, contact Vantive US Healthcare LLC at 1855-857-0003 or FDA at 1-800-FDA-1088 or www.fda.gov/medwatch

FULL PRESCRIBING INFORMATION

1 INDICATIONS AND USAGE

PRISMASOL and PHOXILLUM solutions are indicated in pediatric and adult patients for use as a replacement solution in Continuous Renal Replacement Therapy (CRRT) to replace plasma volume removed by ultrafiltration and to correct electrolyte and acid-base imbalances. They may also be used in case of drug poisoning when CRRT is used to remove dialyzable substances.

2 DOSAGE AND ADMINISTRATION

2.1 Administration Instructions

Visually inspect PRISMASOL and PHOXILLUM for particulate matter and discoloration prior to administration.

Administration should only be under the direction of a physician competent in intensive care treatment including CRRT. Use only with extracorporeal dialysis equipment appropriate for CRRT.

The prepared solution is for single patient use only.

Aseptic technique should be used throughout administration to the patient.

Discard any unused solution.

2.2 Dosing Considerations

PRISMASOL replacement solutions contain 4 different combinations of active ingredients (7 different products with varying ingredient amounts). PHOXILLUM replacement solutions contain 2 different combinations of active ingredients (2 different products with varying ingredient amounts). PRISMASOL and PHOXILLUM are supplied in a two-compartment bag that must be mixed immediately prior to use [see Dosage and Administration (2.3)]:

- Small compartment A (250 mL) containing an electrolyte solution, and
- Large compartment B (4750 mL) containing the buffer solution.

See Table 1for the concentrations of the active ingredients (after mixing) in these 9 different replacement solutions (total volume is 5 Liters).

Table 1: Concentrations of Active Ingredients in the 7 PRISMASOL and 2 PHOXILLUM Replacement Solutions after Mixing
 | Ca^2+ mEq/L | HCO3^- mEq/L | K^+ mEq/L | Mg^2+ mEq/L | Na^+ mEq/L | HPO4^2- mmol/L | Cl^- mEq/L | Lactate mEq/L | Dextrose mg/dL | Osmolarity mOsm/L
PRISMASOL Replacement Solutions
BGK0/2.5 | 2.5 | 32 | 0 | 1.5 | 140 | 0 | 109 | 3 | 100 | 292
BGK4/2.5 | 2.5 | 32 | 4 | 1.5 | 140 | 0 | 113 | 3 | 100 | 300
BGK2/3.5 | 3.5 | 32 | 2 | 1 | 140 | 0 | 111.5 | 3 | 100 | 296
BGK2/0 | 0 | 32 | 2 | 1 | 140 | 0 | 108 | 3 | 100 | 291
B22GK4/0 | 0 | 22 | 4 | 1.5 | 140 | 0 | 120.5 | 3 | 100 | 296
BGK4/0/1.2 | 0 | 32 | 4 | 1.2 | 140 | 0 | 110.2 | 3 | 100 | 295
BK0/0/1.2 | 0 | 32 | 0 | 1.2 | 140 | 0 | 106.2 | 3 | 0 | 282
PHOXILLUM Replacement Solutions
BK4/2.5 | 2.5 | 32 | 4 | 1.5 | 140 | 1 | 114.5 | 0 | 0 | 294
B22K4/0 | 0 | 22 | 4 | 1.5 | 140 | 1 | 122 | 0 | 0 | 290
Ca^2+= calcium, HCO3^-= bicarbonate, K^+= potassium, Mg^2+= magnesium, Na^+= sodium, HPO4^2-= phosphate, Cl- = chloride; osmolarity is estimated

The mode of therapy, solute formulation, flow rates, and length of PRISMASOL and PHOXILLUM replacement therapy in CRRT should be established by a physician based on the patient’s clinical condition, blood concentration of phosphate and other electrolytes, acid-base and glucose balance. Administer either PRISMASOL or PHOXILLUM into the extracorporeal circuit:

- Before (pre-dilution) the hemofilter or hemodiafilter,
- After (post-dilution) the hemofilter or hemodiafilter, or
- Before and after the hemofilter or hemodiafilter.

2.3 Preparing the Solution

Use only if the overwrap is not damaged, all seals are intact, peel seal is not broken, and the solution is clear.

The solution may be warmed to 37°C/98.6°F prior to removing the overwrap to enhance patient comfort. However, only dry heat should be used. Solutions should not be heated in water or in a microwave oven. After heating, verify that the solution remains clear and contains no particulate matter.

The solutions are supplied in two different two-compartment bags made of polyolefin with a peel seal separating compartment A and B (see Figure 1).

Follow the instructions below when connecting the solution bags for correct use of the access ports.

Instructions for preparing solutions supplied in a two-compartment, polyolefin bag with a peel seal:

Figure 2

Step 1Immediately before use, remove the overwrap from the bag and mix the solutions in the two different compartments. After removing the overwrap, inspect the bag for leakage by pressing firmly on the bag. Discard the bag if any leakage is detected since sterility cannot be assured. As soon as the overwrap is removed, the reconstitution of compartments A and B should be done and the mixed solution should be used immediately.

After removal of the overwrap, the solution is stable for 24 hours including the duration of the treatment.

Hold the small compartment with both hands and squeeze it until an opening is created in the peel seal. (See Figure 2beside)

Figure 3

Step 2Squeeze with both hands on the large compartment until the peel seal between the two compartments is entirely open. Shake gently to mix. (See Figure 3beside)

The solution is now ready to use and the bag can be hung on the equipment.

Figure 4a

Step 3The replacement line may be connected to the bag through either of the luer connector or the injection connector (spike connector).

Step 3aThe luer connector is a needle-less and swabbable connector. Remove the cap with a twist and pull motion, and connect the male luer lock on the replacement line to the female luer receptor on the bag. (See Figure 4a beside)

Ensure that the connection is fully seated and tighten. The connector is now open. Verify that the fluid is flowing freely during use.

When the replacement line is disconnected from the luer connector, the connector will close and the flow of the solution will stop.

Figure 4b

Step 3bIf the injection connector (spike connector) is used, first remove the snap-off cap. Then introduce the replacement line spike through the swabbable rubber septum of the bag connector. (See Figure 4b beside)

Ensure that the spike is fully inserted and verify that the fluid is flowing freely during use.

2.4 Adding Drugs to the Solutions

After mixing, additional drugs may be added to the bag via injection connector (spike connector) in large compartment B. In general, administer drugs other than phosphate through a different access line.

When introducing drugs, use aseptic techniques and mix thoroughly prior to connecting the solution bag to the extracorporeal circuit.

Do not use if there is a color change and/or the appearance of precipitates, insoluble complexes or crystals after addition of medication.

Phosphate: Up to 1.2 mmol/L of phosphate can be added to the bag as potassium phosphate or sodium phosphate. The total potassium concentration of PRISMASOL solution should not exceed 4 mEq/L. Use sodium phosphate to add phosphate if the total potassium concentration in PRISMASOL solution is 4 mEq/L.

PHOXILLUM Solutions:

Phosphate:Phosphate up to 0.2 mmol/L may be added to the solution. Use sodium phosphate if adding phosphate to bag. The total phosphate concentration should not exceed 1.2 mmol/L.

3 DOSAGE FORMS AND STRENGTHS

See Table 1for the concentrations of the active ingredients (after mixing) in these 9 different replacement solutions [see Dosage and Administration (2.2)] .

4 CONTRAINDICATIONS

PHOXILLUM and PRISMASOL replacement solutions are contraindicated in patients with known hypersensitivities to these products.

5 WARNINGS AND PRECAUTIONS

5.1 Electrolyte and Volume Abnormalities

PHOXILLUM and PRISMASOL solutions can affect electrolytes and volume and may result in hyperkalemia or hyperphosphatemia. Monitor hemodynamic status and fluid inputs and outputs, potassium, phosphorous, calcium, other electrolytes and acid-base balance throughout the procedure. Abnormalities may be corrected by changing the formulation of replacement solution and/or dialysate, supplementation, or adjusting flow rates appropriately [ see Dosage and Administration (2)].

PHOXILLUM replacement solutions contain hydrogen phosphate, a weak acid that may increase the risk of metabolic acidosis.

5.2 Blood Glucose Abnormalities

The use of PRISMASOL and PHOXILLUM replacement solutions can affect blood glucose levels resulting in hypo- or hyper-glycemia depending upon the dextrose content of the replacement solution. Monitor blood glucose levels regularly. Patients may require initiation of or modification of antidiabetic therapy or other corrective measures during treatment.

6 ADVERSE REACTIONS

The following adverse reactions have been identified during postapproval use with these or other similar products and therefore may occur with use of PHOXILLUM or PRISMASOL. Because these reactions are reported voluntarily from a population of uncertain size, it is not always possible to reliably estimate their frequency or establish a causal relationship to drug exposure.

- Metabolic acidosis
- Hypotension
- Acid-base disorders
- Electrolyte imbalance including calcium ionized increased (reported in PRISMASOL solutions containing calcium), hyperphosphatemia, and hypophosphatemia
- Fluid imbalance

7 DRUG INTERACTIONS

As with the use of other replacement solutions, blood concentrations of dialyzable drugs may be reduced by CRRT due to their removal by the hemofilter or hemodiafilter. The blood concentrations of certain drugs may need to be monitored and appropriate therapy implemented to correct for removal during treatment.

7.1 Citrate

When used as an anticoagulant, citrate contributes to the overall buffer load and can reduce plasma calcium levels. Select the PRISMASOL/PHOXILLUM formulation(s) accordingly.

8 USE IN SPECIFIC POPULATIONS

8.1 Pregnancy

Risk Summary

PRISMASOL and PHOXILLUM are pharmacologically inactive solutions. While there are no adequate and well controlled studies in pregnant women, appropriate administration of PRISMASOL and PHOXILLUM solutions with monitoring of fluid, electrolyte, acid-base and glucose balance, is not expected to cause fetal harm. Animal reproduction studies have not been conducted with PRISMASOL and PHOXILLUM solutions.

The estimated background risk of major birth defects and miscarriage for the indicated population are unknown. All pregnancies have a background risk of birth defect, loss or other adverse outcomes. In the U.S. general population, the estimated background risk of major birth defects and miscarriage in clinically recognized pregnancies is 2 to 4% and 15 to 20%, respectively.

Clinical Considerations

Maintenance of normal acid-base balance is important for fetal well-being.

8.2 Lactation

Risk Summary

The components of PRISMASOL and PHOXILLUM solutions are excreted in human milk. Appropriate administration of PRISMASOL and PHOXILLUM solutions with monitoring of fluid, electrolyte, acid-base and glucose balance, is not expected to harm a nursing infant.

8.4 Pediatric Use

Safety and effectiveness have been established based on published clinical data of CRRT replacement solutions with compositions similar to PRISMASOL and PHOXILLUM used in adults and two hemofiltration studies in pediatric patients, including a study of newborns to 17 years old.

8.5 Geriatric Use

The experience with PRISMASOL and PHOXILLUM solutions in geriatric patients has not identified novel concerns.

11 DESCRIPTION

PRISMASOL and PHOXILLUM solutions are clear, sterile, free of bacterial endotoxins and contain no bacteriostatic or antimicrobial agents. These solutions are used in Continuous Renal Replacement Therapies (CRRT) as a replacement solution in hemofiltration and hemodiafiltration. Depending on the product (see Table 2), the two compartments contain:

Calcium chloride, USP, is chemically designated calcium chloride dihydrate (CaCl2• 2H2O).

Magnesium chloride, USP, is chemically designated magnesium chloride hexahydrate (MgCl2• 6H2O).

Sodium chloride, USP, is chemically designated NaCl.

Potassium chloride, USP, is chemically designated KCl.

Sodium bicarbonate, USP, is chemically designated NaHCO3.

Dextrose, USP, is chemically designated D-Glucose anhydrous (C6H12O6) or D-Glucose monohydrate (C6H12O6• H2O).

Lactic acid, USP, is chemically designated CH3CH(OH)COOH.

Dibasic sodium phosphate, USP, is chemically designated as disodium hydrogen phosphate, dihydrate (Na2HPO4• 2H2O)

Table 2 - Compartment Composition (Before Mixing)
 | Compartment A (g/L) |  |  |  | Compartment B (g/L)
 | Calcium Chloride ∙ 2H2O | Magnesium Chloride ∙ 6H2O | Dextrose anhydrous (as monohydrate) | Lactic Acid | Sodium Chloride | Sodium bicarbonate | Potassium Chloride | Sodium Phosphate ∙ 2H2O
PRISMASOL SOLUTIONS
BGK 0/2.5 | 3.68 | 3.05 | 20 (22) | 5.40 | 6.46 | 3.09 | 0 | 0
BGK 4/2.5 | 3.68 | 3.05 | 20 (22) | 5.40 | 6.46 | 3.09 | 0.314 | 0
BGK 2/3.5 | 5.15 | 2.03 | 20 (22) | 5.40 | 6.46 | 3.09 | 0.157 | 0
BGK 2/0 | 0 | 2.03 | 20 (22) | 5.40 | 6.46 | 3.09 | 0.157 | 0
B22GK 4/0 | 0 | 3.05 | 20 (22) | 5.40 | 7.07 | 2.21 | 0.314 | 0
BK 0/0/1.2 | 0 | 2.44 | 0 (0) | 5.40 | 6.46 | 3.09 | 0 | 0
BGK 4/0/1.2 | 0 | 2.44 | 20 (22) | 5.40 | 6.46 | 3.09 | 0.314 | 0
PHOXILLUM SOLUTIONS
BK 4/2.5 | 3.68 | 3.05 | 0 (0) | 0 | 6.34 | 3.09 | 0.314 | 0.187
B22K 4/0 | 0 | 3.05 | 0 (0) | 0 | 6.95 | 2.21 | 0.314 | 0.187

The pH of the final solution is in the range of 7.0 to 8.5.

12 CLINICAL PHARMACOLOGY

12.1 Mechanism of Action

PRISMASOL and PHOXILLUM solutions are pharmacologically inactive. The electrolyte concentrations in the solutions are chosen to restore plasma levels to clinically desired concentrations or maintain plasma levels at the desired concentrations.

PRISMASOL and PHOXILLUM solutions are used as replacement solution to replace water and electrolytes removed during hemofiltration and hemodiafiltration. Bicarbonate (or precursor lactate) in the solution is used as an alkalinizing buffer to restore acid-base balance to a clinically desirable level.

12.3 Pharmacokinetics

The distribution of electrolytes, bicarbonate, and dextrose is determined by the patient's clinical condition, metabolic status, and residual renal function.

The elimination and replacement of water, electrolytes and buffer depend on the patient's electrolyte and acid-base balance, metabolic status, residual renal function and ongoing physiologic losses through intestinal, respiratory and cutaneous routes.

16 HOW SUPPLIED/STORAGE AND HANDLING

PRISMASOL and PHOXILLUM solutions are supplied in a two-compartment bag made of polyolefin. The 5000 mL bag is composed of a small compartment (250 mL) and a large compartment (4750 mL). The two compartments are separated by a peel seal.

The bag is overwrapped with a transparent overwrap. See Table 2for the concentrations of the active ingredients in each compartment for each product [see Description (11)].

Container | Fill Volume | NDC
PRISMASOL Solutions
PRISMASOL BGK0/2.5 | 5000 mL | 24571-108-06
PRISMASOL BGK4/2.5 | 5000 mL | 24571-105-06
PRISMASOL BGK2/3.5 | 5000 mL | 24571-103-06
PRISMASOL BGK2/0 | 5000 mL | 24571-102-06
PRISMASOL B22GK4/0 | 5000 mL | 24571-111-06
PRISMASOL BK0/0/1.2 | 5000 mL | 24571-113-06
PRISMASOL BGK4/0/1.2 | 5000 mL | 24571-114-06
PHOXILLUM Solutions
PHOXILLUM BK4/2.5 | 5000 mL | 24571-116-06
PHOXILLUM B22K4/0 | 5000 mL | 24571-117-06

Not all formulations may be marketed.

Storage conditions

Store at 20°C to 25°C (68°F to 77°F); excursions permitted to 15ºC to 30ºC (59ºF to 86ºF). [See USP Controlled Room Temperature]

Do not freeze or expose to excessive heat. Do not use if precipitate has formed or if container seals have been damaged.

Manufactured for:
Vantive US Healthcare LLC
One Baxter Parkway
Deerfield, Illinois 60015

07-19-00-8247

Vantive, Phoxillum and PrismaSol are trademarks of Vantive Health Inc., or its subsidiaries

Package/Label Display Panel

Mixing steps

① SQUEEZE TOPcorners to break seal

②Squeeze BAG SIDESto fully open seal

Barcode
NDC# 24571-108-06

OK^+
mEq/L

2.5 Ca^2+
mEq/L

PrismaSol BGK0/2.5
Rx only
Barcode
Replacement Solution for Continuous Renal Replacement Therapy

Before reconstitution each 1000 mL contains (g) | A | B
Calcium chloride • 2H2O | 3.68
Magnesium chloride • 6H2O | 3.05
Dextrose anhydrous | 20.0
(as dextrose monohydrate) | 22.0
Sodium chloride |  | 6.46
Lactic acid | 5.40
Sodium bicarbonate |  | 3.09
Water for injections q.s, Carbon dioxide for pH adjustment

A
250 mL

B
4750 mL

After reconstitution, A + B
 | Calcium Ca^2+ | Magnesium Mg^2+ | Sodium Na^+ | Chloride Cl^- | Lactate C3H5O3^- | Bicarbonate HCO3^- | Potassium K^+ | Dextrose
mmol/L | 1.25 | 0.75 | 140 | 109.0 | 3.0 | 32 | 0 | 5.5
mEq/L | 2.5 | 1.5 | 140 | 109.0 | 3.0 | 32 | 0 | (100 mg/dL)
- Theoretical osmolarity: 292 mOsm/L pH: 7.0 – 8.5

Mix both compartments before use.
See package insert for dosage information and

further instructions.

Sterile and free from bacterial endotoxins.

Confirm the integrity of the packaging. Use only if

solution is clear. For single use only.

DISCARD ANY UNUSED SOLUTION.

Store at +20°C to +25°C (+68°F to +77°F); excursions

permitted to +15°C to +30°C (+59°F to

+86°F). [See USP Controlled room Temperature.]

Do not freeze or expose to excessive heat.

As soon as the overwrap is removed, the reconstitution

of compartments A and B should be done

and the reconstituted solution should be used immediately.

After removal of the overwrap, the solution

is stable for 24 hours including the duration of

the treatment. Mix additives BEFORE connecting

this bag to the extracorporeal circuit. (See insert

for further information.) This product is not made

with natural rubber latex.

5000 mL
EAN-14: 07332414091613
Product # 110240

VANTIVE Logo

Batch No. and expiry date are printed on the back of the bag.
Manufactured for:
Vantive US Healthcare LLC
Deerfield IL 60015 USA
Made in Italy

REPLACEMENT
Solution for Continuous Renal Replacement Therapy

07-25-00-5278

Mixing steps

① SQUEEZE TOPcorners to break seal

②Squeeze BAG SIDESto fully open seal

Barcode
NDC# 24571-105-06

4K^+
mEq/L

2.5 Ca^2+
mEq/L

PrismaSol BGK4/2.5
Rx only
Barcode
Replacement Solution for Continuous Renal Replacement Therapy

Before reconstitution each 1000 mL contains (g) | A | B
Calcium chloride • 2H2O | 3.68
Magnesium chloride • 6H2O | 3.05
Dextrose anhydrous | 20.0
(as dextrose monohydrate) | 22.0
Sodium chloride |  | 6.46
Potassium chloride |  | 0.314
Lactic acid | 5.40
Sodium bicarbonate |  | 3.09
Water for injections q.s, Carbon dioxide for pH adjustment

A
250 mL

B
4750 mL

After reconstitution, A + B
 | Calcium Ca^2+ | Magnesium Mg^2+ | Sodium Na^+ | Chloride Cl^- | Lactate C3H5O3^- | Bicarbonate HCO3^- | Potassium K^+ | Dextrose
mmol/L | 1.25 | 0.75 | 140 | 113.0 | 3.0 | 32 | 4.0 | 5.5
mEq/L | 2.5 | 1.5 | 140 | 113.0 | 3.0 | 32 | 4.0 | (100 mg/dL)
- Theoretical osmolarity: 300 mOsm/L pH: 7.0 – 8.5

Mix both compartments before use.
See package insert for dosage information and

further instructions.

Sterile and free from bacterial endotoxins.

Confirm the integrity of the packaging. Use only if

solution is clear. For single use only.

DISCARD ANY UNUSED SOLUTION.

Store at +20°C to +25°C (+68°F to +77°F); excursions

permitted to +15°C to +30°C (+59°F to

+86°F). [See USP Controlled room Temperature.]

Do not freeze or expose to excessive heat.

As soon as the overwrap is removed, the reconstitution

of compartments A and B should be done

and the reconstituted solution should be used immediately.

After removal of the overwrap, the solution

is stable for 24 hours including the duration of

the treatment. Mix additives BEFORE connecting

this bag to the extracorporeal circuit. (See insert

for further information.) This product is not made

with natural rubber latex.

5000 mL
EAN-14: 07332414091637
Product # 110242

VANTIVE Logo

Batch No. and expiry date are printed on the back of the bag.
Manufactured for:
Vantive US Healthcare LLC
Deerfield IL 60015 USA
Made in Italy

REPLACEMENT
Solution for Continuous Renal Replacement Therapy
07-25-00-5280

Mixing steps

① SQUEEZE TOPcorners to break seal

②Squeeze BAG SIDESto fully open seal

Barcode
NDC# 24571-103-06

2K^+
mEq/L

3.5 Ca^2+
mEq/L

PrismaSol BGK2/3.5
Rx only
Barcode
Replacement Solution for Continuous Renal Replacement Therapy

Before reconstitution each 1000 mL contains (g) | A | B
Calcium chloride • 2H2O | 5.15
Magnesium chloride • 6H2O | 2.03
Dextrose anhydrous | 20.0
(as dextrose monohydrate) | 22.0
Sodium chloride |  | 6.46
Potassium chloride |  | 0.157
Lactic acid | 5.40
Sodium bicarbonate |  | 3.09
Water for injections q.s, Carbon dioxide for pH adjustment

Rx only
A
250 mL

B
4750 mL

After reconstitution, A + B
 | Calcium Ca^2+ | Magnesium Mg^2+ | Sodium Na^+ | Chloride Cl^- | Lactate C3H5O3^- | Bicarbonate HCO3^- | Potassium K^+ | Dextrose
mmol/L | 1.75 | 0.5 | 140 | 111.5 | 3.0 | 32 | 2.0 | 5.5
mEq/L | 3.5 | 1.0 | 140 | 111.5 | 3.0 | 32 | 2.0 | (100 mg/dL)
- Theoretical osmolarity: 296 mOsm/L pH: 7.0 – 8.5

Mix both compartments before use.
See package insert for dosage information and

further instructions.

Sterile and free from bacterial endotoxins.

Confirm the integrity of the packaging. Use only if

solution is clear. For single use only.

DISCARD ANY UNUSED SOLUTION.

Store at +20°C to +25°C (+68°F to +77°F); excursions

permitted to +15°C to +30°C (+59°F to

+86°F). [See USP Controlled room Temperature.]

Do not freeze or expose to excessive heat.

As soon as the overwrap is removed, the reconstitution

of compartments A and B should be done

and the reconstituted solution should be used immediately.

After removal of the overwrap, the solution

is stable for 24 hours including the duration of

the treatment. Mix additives BEFORE connecting

this bag to the extracorporeal circuit. (See insert

for further information.) This product is not made

with natural rubber latex.

5000 mL
EAN-14: 07332414091644
Product # 110243

VANTIVE Logo

Batch No. and expiry date are printed on the back of the bag.
Manufactured for:
Vantive US Healthcare LLC
Deerfield IL 60015 USA
Made in Italy

REPLACEMENT
Solution for Continuous Renal Replacement Therapy
07-25-00-5281

Mixing steps

① SQUEEZE TOPcorners to break seal

②Squeeze BAG SIDESto fully open seal

Barcode
NDC# 24571-102-06

2K^+
mEq/L

0Ca^2+
mEq/L

PrismaSol BGK2/0
Rx only
Barcode
Replacement Solution for Continuous Renal Replacement Therapy

Before reconstitution each 1000 mL contains (g) | A | B
Magnesium chloride • 6H2O | 2.03
Dextrose anhydrous | 20.0
(as dextrose monohydrate) | 22.0
Sodium chloride |  | 6.46
Potassium chloride |  | 0.157
Lactic acid | 5.40
Sodium bicarbonate |  | 3.09
Water for injections q.s, Carbon dioxide for pH adjustment

A
250 mL

B
4750 mL

After reconstitution, A + B
 | Calcium Ca^2+ | Magnesium Mg^2+ | Sodium Na^+ | Chloride Cl^- | Lactate C3H5O3^- | Bicarbonate HCO3^- | Potassium K^+ | Dextrose
mmol/L | 0 | 0.5 | 140 | 108.0 | 3.0 | 32 | 2.0 | 5.5
mEq/L | 0 | 1.0 | 140 | 108.0 | 3.0 | 32 | 2.0 | (100 mg/dL)
- Theoretical osmolarity: 291 mOsm/L pH: 7.0 – 8.5

Mix both compartments before use.
See package insert for dosage information and

further instructions.

Sterile and free from bacterial endotoxins.

Confirm the integrity of the packaging. Use only if

solution is clear. For single use only.

DISCARD ANY UNUSED SOLUTION.

Store at +20°C to +25°C (+68°F to +77°F); excursions

permitted to +15°C to +30°C (+59°F to

+86°F). [See USP Controlled room Temperature.]

Do not freeze or expose to excessive heat.

As soon as the overwrap is removed, the reconstitution

of compartments A and B should be done

and the reconstituted solution should be used immediately.

After removal of the overwrap, the solution

is stable for 24 hours including the duration of

the treatment. Mix additives BEFORE connecting

this bag to the extracorporeal circuit. (See insert

for further information.) This product is not made

with natural rubber latex.

5000 mL
EAN-14: 07332414091651
Product # 110244

VANTIVE Logo

Batch No. and expiry date are printed on the back of the bag.
Manufactured for:
Vantive US Healthcare LLC
Deerfield IL 60015 USA
Made in Italy

REPLACEMENT
Solution for Continuous Renal Replacement Therapy

07-25-00-5282

Mixing steps

① SQUEEZE TOPcorners to break seal

②Squeeze BAG SIDESto fully open seal

Barcode
NDC# 24571-111-06

4K^+
mEq/L

Bicarbonate 22

0Ca^2+
mEq/L

PrismaSol B22GK4/0
Rx only
Barcode
Replacement Solution for Continuous Renal Replacement Therapy

Before reconstitution each 1000 mL contains (g) | A | B
Magnesium chloride • 6H2O | 3.05
Dextrose anhydrous | 20.0
(as dextrose monohydrate) | 22.0
Sodium chloride |  | 7.07
Potassium chloride |  | 0.314
Lactic acid | 5.40
Sodium bicarbonate |  | 2.21
Water for injections q.s, Carbon dioxide for pH adjustment

A
250 mL

B
4750 mL

After reconstitution, A + B
 | Calcium Ca^2+ | Magnesium Mg^2+ | Sodium Na^+ | Chloride Cl^- | Lactate C3H5O3^- | Bicarbonate HCO3^- | Potassium K^+ | Dextrose
mmol/L | 0 | 0.75 | 140 | 120.5 | 3.0 | 22 | 4.0 | 5.5
mEq/L | 0 | 1.5 | 140 | 120.5 | 3.0 | 22 | 4.0 | (100 mg/dL)
- Theoretical osmolarity: 296 mOsm/L pH: 7.0 – 8.5

Mix both compartments before use.
See package insert for dosage information and

further instructions.

Sterile and free from bacterial endotoxins.

Confirm the integrity of the packaging. Use only if

solution is clear. For single use only.

DISCARD ANY UNUSED SOLUTION.

Store at +20°C to +25°C (+68°F to +77°F); excursions

permitted to +15°C to +30°C (+59°F to

+86°F). [See USP Controlled room Temperature.]

Do not freeze or expose to excessive heat.

As soon as the overwrap is removed, the reconstitution

of compartments A and B should be done

and the reconstituted solution should be used immediately.

After removal of the overwrap, the solution

is stable for 24 hours including the duration of

the treatment. Mix additives BEFORE connecting

this bag to the extracorporeal circuit. (See insert

for further information.) This product is not made

with natural rubber latex.

5000 mL
EAN-14: 07332414116781
Product # 115001

VANTIVE Logo

Batch No. and expiry date are printed on the back of the bag.
Manufactured for:
Vantive US Healthcare LLC
Deerfield IL 60015 USA
Made in Italy

REPLACEMENT
Solution for Continuous Renal Replacement Therapy

07-25-00-5285

Mixing steps

① SQUEEZE TOPcorners to break seal

②Squeeze BAG SIDESto fully open seal

Barcode
NDC# 24571-113-06

0K^+
mEq/L

0Ca^2+
mEq/L

PrismaSol BK0/0/1.2
Rx only
Barcode
Replacement Solution for Continuous Renal Replacement Therapy

Before reconstitution each 1000 mL contains (g) | A | B
Magnesium chloride • 6H2O | 2.44
Sodium chloride |  | 6.46
Lactic acid | 5.40
Sodium bicarbonate |  | 3.09
Water for injections q.s, Carbon dioxide for pH adjustment

A
250 mL

B
4750 mL

After reconstitution, A + B
 | Calcium Ca^2+ | Magnesium Mg^2+ | Sodium Na^+ | Chloride Cl^- | Lactate C3H5O3^- | Bicarbonate HCO3^- | Potassium K^+ | Dextrose
mmol/L | 0 | 0.6 | 140 | 106.2 | 3.0 | 32 | 0 | 0
mEq/L | 0 | 1.2 | 140 | 106.2 | 3.0 | 32 | 0 | (0 mg/dL)
- Theoretical osmolarity: 282 mOsm/L pH: 7.0 – 8.5

Mix both compartments before use.
See package insert for dosage information and

further instructions.

Sterile and free from bacterial endotoxins.

Confirm the integrity of the packaging. Use only if

solution is clear. For single use only.

DISCARD ANY UNUSED SOLUTION.

Store at +20°C to +25°C (+68°F to +77°F); excursions

permitted to +15°C to +30°C (+59°F to

+86°F). [See USP Controlled room Temperature.]

Do not freeze or expose to excessive heat.

As soon as the overwrap is removed, the reconstitution

of compartments A and B should be done

and the reconstituted solution should be used immediately.

After removal of the overwrap, the solution

is stable for 24 hours including the duration of

the treatment. Mix additives BEFORE connecting

this bag to the extracorporeal circuit. (See insert

for further information.) This product is not made

with natural rubber latex.

5000 mL
EAN-14: 07332414091309
Product # 110239

VANTIVE Logo

Batch No. and expiry date are printed on the back of the bag.
Manufactured for:
Vantive US Healthcare LLC
Deerfield IL 60015 USA
Made in Italy

REPLACEMENT
Solution for Continuous Renal Replacement Therapy

07-25-00-5277

Mixing steps

① SQUEEZE TOPcorners to break seal

②Squeeze BAG SIDESto fully open seal

Barcode
NDC# 24571-114-06

4K^+
mEq/L

0Ca^2+
mEq/L

PrismaSol BGK4/0/1.2
Rx only
Barcode
Replacement Solution for Continuous Renal Replacement Therapy

Before reconstitution each 1000 mL contains (g) | A | B
Magnesium chloride • 6H2O | 2.44
Dextrose anhydrous | 20.0
(as dextrose monohydrate) | 22.0
Sodium chloride |  | 6.46
Potassium chloride |  | 0.314
Lactic acid | 5.40
Sodium bicarbonate |  | 3.09
Water for injections q.s, Carbon dioxide for pH adjustment

A
250 mL

B
4750 mL

After reconstitution, A + B
 | Calcium Ca^2+ | Magnesium Mg^2+ | Sodium Na^+ | Chloride Cl^- | Lactate C3H5O3^- | Bicarbonate HCO3^- | Potassium K^+ | Dextrose
mmol/L | 0 | 0.6 | 140 | 110.2 | 3.0 | 32 | 4.0 | 5.5
mEq/L | 0 | 1.2 | 140 | 110.2 | 3.0 | 32 | 4.0 | (100 mg/dL)
- Theoretical osmolarity: 295 mOsm/L pH: 7.0 – 8.5

Mix both compartments before use.
See package insert for dosage information and

further instructions.

Sterile and free from bacterial endotoxins.

Confirm the integrity of the packaging. Use only if

solution is clear. For single use only.

DISCARD ANY UNUSED SOLUTION.

Store at +20°C to +25°C (+68°F to +77°F); excursions

permitted to +15°C to +30°C (+59°F to

+86°F). [See USP Controlled room Temperature.]

Do not freeze or expose to excessive heat.

As soon as the overwrap is removed, the reconstitution

of compartments A and B should be done

and the reconstituted solution should be used immediately.

After removal of the overwrap, the solution

is stable for 24 hours including the duration of

the treatment. Mix additives BEFORE connecting

this bag to the extracorporeal circuit. (See insert

for further information.) This product is not made

with natural rubber latex.

5000 mL
EAN-14: 07332414091620
Product # 110241

VANTIVE Logo

Batch No. and expiry date are printed on the back of the bag.
Manufactured for:
Vantive US Healthcare LLC
Deerfield IL 60015 USA
Made in Italy

REPLACEMENT
Solution for Continuous Renal Replacement Therapy

07-25-00-5279

Mixing steps
① SQUEEZE TOPcorners to break seal

②Squeeze BAG SIDESto fully open seal

Compartment B

Barcode
NDC# 24571-116-06

4K^+
mEq/L

1 Phosphate
mmol/L

2.5 Ca^2+
mEq/L

Phoxillum BK4/2.5
Replacement Solution for Continuous Renal Replacement Therapy

Before reconstitution, each 1000 mL contains (g): | A | B
Calcium chloride • 2H2O | 3.68
Magnesium chloride • 6H2O | 3.05
Sodium chloride |  | 6.34
Potassium chloride |  | 0.314
Sodium bicarbonate |  | 3.09
Dibasic sodium phosphate • 2H2O |  | 0.187
Water for injections q.s

Rx only
A
250 mL

B
4750 mL

After reconstitution, A + B

 | Calcium Ca^2+ | Magnesium Mg^2+ | Sodium Na^+ | Chloride Cl^- | Bicarbonate HCO3^- | Potassium K^+ | Phosphate HPO4^2- | Dextrose
mmol/L | 1.25 | 0.75 | 140 | 114.5 | 32 | 4.0 | 1 | 0
mEq/L | 2.5 | 1.5 | 140 | 114.5 | 32 | 4.0 | (1 mmol/L) | (0 mg/dL)

- Theoretical osmolarity: 294 mOsm/L pH: 7.0 – 8.5

Mix both compartments before use.
See package insert for dosage information and further instructions. Sterile and free from bacterial endotoxins.
Confirm the integrity of the packaging. Use only if solution is clear. For single use only. DISCARD ANY UN-
USED SOLUTION. Store at +20ºC to +25ºC (+68ºF to +77ºF); excursions permitted to +15ºC - +30ºC (+59ºF
to +86ºF). [See USP Controlled Room Temperature]. Do not freeze or expose to excessive heat. As soon as the
overwrap is removed, the reconstitution of compartments A and B should be done and the reconstituted
solution should be used immediately. After removal of the overwrap, the solution is stable for 24 hours including the duration of the treatment. Mix additives BEFORE connecting this bag to the extracorporeal circuit. (See insert for
further information.) This product is not made with natural rubber latex. Carbon dioxide and diluted hydrochloric

acid added for pH adjustment.

5000 mL
EAN-14: 07332414116040
Product # 114905

VANTIVE Logo

Batch No. and expiry date are printed on the back of the bag.
Manufactured for:
Vantive US Healthcare LLC
Deerfield IL 60015 USA
Made in Italy

REPLACEMENT
Solution for Continuous Renal Replacement Therapy

07-25-00-5283

Mixing steps

① SQUEEZE TOPcorners to break seal

②Squeeze BAG SIDESto fully open seal

Compartment B

Barcode
NDC# 24571-117-06

4K^+
mEq/L

0 Ca^2+
mEq/L

22 Bicarbonate
mEq/L

1 Phosphate
mmol/L

Phoxillum B22K4/0
Replacement Solution for Continuous Renal Replacement Therapy

Before reconstitution, each 1000 mL contains (g): | A | B
Magnesium chloride • 6H2O | 3.05
Sodium chloride |  | 6.95
Potassium chloride |  | 0.314
Sodium bicarbonate |  | 2.21
Dibasic sodium phosphate • 2H2O |  | 0.187
Water for injections q.s

Rx only
A
250 mL

B
4750 mL

After reconstitution, A + B

 | Calcium Ca^2+ | Magnesium Mg^2+ | Sodium Na^+ | Chloride Cl^- | Bicarbonate HCO3^- | Potassium K^+ | Phosphate HPO4^2- | Dextrose
mmol/L | 0 | 0.75 | 140 | 122.0 | 22 | 4.0 | 1 | 0
mEq/L | 0 | 1.5 | 140 | 122.0 | 22 | 4.0 | (1 mmol/L) | (0 mg/dL)

- Theoretical osmolarity: 290 mOsm/L pH: 7.0 – 8.5

Mix both compartments before use.

See package insert for dosage information and further instructions. Sterile and free from bacterial endotoxins.
Confirm the integrity of the packaging. Use only if solution is clear. For single use only. DISCARD ANY UN-
USED SOLUTION. Store at +20°C to +25°C (+68°F to +77°F); excursions permitted to +15°C to +30°C (+59°F
to +86°F). [See USP Controlled Room Temperature]. Do not freeze or expose to excessive heat. As soon as the
overwrap is removed, the reconstitution of compartments A and B should be done and the reconstituted solution
should be used immediately. After removal of the overwrap, the solution is stable for 24 hours including the duration
of the treatment. Mix additives BEFORE connecting this bag to the extracorporeal circuit. (See insert for
further information.) This product is not made with natural rubber latex. Carbon dioxide and diluted hydrochloric
acid added for pH adjustment.

5000 mL
EAN-14: 07332414116057
Product # 114906

VANTIVE Logo

Batch No. and expiry date are printed on the back of the bag.
Manufactured for:
Vantive US Healthcare LLC
Deerfield IL 60015 USA
Made in Italy

REPLACEMENT
Solution for Continuous Renal Replacement Therapy

07-25-00-5284

IFU Label

HIGHLIGHTS OF PRESCRIBING INFORMATION

These highlights do not include all the information needed to use PRISMASOL and PHOXILLUM safely and effectively.
See full prescribing information for PRISMASOL and PHOXILLUM.
PRISMASOL renal replacement solution PRISMASOL Initial U.S. Approval: 2006
PHOXILLUM renal replacement solution PHOXILLUM Initial U.S. Approval: 2015
-------------INDICATIONS AND USAGE-------------

PRISMASOL and PHOXILLUM solutions are indicated:
• As a replacement solution in Continuous Renal Replacement Therapy (CRRT) and in case of drug poisoning when CRRT is used to remove dialyzable substances (1)
---------DOSAGE AND ADMINISTRATION---------

• Therapy must be individualized based on the patient’s clinical condition, fluid, electrolyte, acid-base and glucose balance (2.2)
• Solution must be mixed prior to use (2.2)
• Use only with extracorporeal dialysis equipment appropriate for CRRT (2.3)

------------- DOSAGE FORMS AND STRENGTHS----------

PRISMASOL and PHOXILLUM are available in multiple combinations of ingredients and in multiple variations of strengths. See full Prescribing Information for detailed descriptions of each formulation. (2, 3, 11)

-------------- CONTRAINDICATIONS-----------------

• Known hypersensitivities to PRISMASOL and PHOXILLUM solutions (4)

--------- WARNINGS AND PRECAUTIONS--------

• Monitor hemodynamic status and fluid inputs and outputs, potassium, phosphorus, other electrolytes and acid-base balance. Abnormalities may be corrected by the use of appropriate formulations and dosage of PRISMASOL and PHOXILLUM solutions (5.1)

• Treatment may affect glucose levels. Monitor blood glucose levels. Antidiabetic therapy adjustment or other corrective measures may be required during treatment (5.2)

To report SUSPECTED ADVERSE REACTIONS, contact Vantive US Healthcare LLC at 1-855-857-0003 or FDA at 1-800-FDA-1088 or www.fda.gov/medwatch

Revised: 10/2024

FULL PRESCRIBING INFORMATION: CONTENTS*

1 INDICATIONS AND USAGE

2 DOSAGE AND ADMINISTRATION

1. 2.1 Administration Instructions
2. 2.2 Dosing Considerations
3. 2.3 Preparing the Solution
4. 2.4 Adding Drugs to the Solutions

3 DOSAGE FORMS AND STRENGTHS

4 CONTRAINDICATIONS

5 WARNINGS AND PRECAUTIONS

1. 5.1 Electrolyte and Volume Abnormalities
2. 5.2 Blood Glucose Abnormalities

6 ADVERSE REACTIONS

7 DRUG INTERACTIONS

1. 7.1 Citrate

07-19-00-8247

8 USE IN SPECIFIC POPULATIONS

1. 8.1 Pregnancy
2. 8.2 Lactation
3. 8.4 Pediatric Use
4. 8.5 Geriatric Use

11 DESCRIPTION

12 CLINICAL PHARMACOLOGY

1. 12.1 Mechanism of Action
2. 12.3 Pharmacokinetics

16 HOW SUPPLIED/STORAGE AND HANDLING

*Sections or subsections omitted from the full prescribing information are not listed.

1. Vantive Logo

FULL PRESCRIBING INFORMATION

1 INDICATIONS AND USAGE

PRISMASOL and PHOXILLUM solutions are indicated in pediatric and adult patients for use as a replacement solution in Continuous Renal Replacement Therapy (CRRT) to replace plasma volume removed by ultrafiltration and to correct electrolyte and acid-base imbalances. They may also be used in case of drug poisoning when CRRT is used to remove dialyzable substances.

2 DOSAGE AND ADMINISTRATION

2.1 Administration Instructions
Visually inspect PRISMASOL and PHOXILLUM for particulate matter and discoloration prior to administration. Administration should only be under the direction of a physician competent in intensive care treatment including CRRT. Use only with extracorporeal dialysis equipment appropriate for CRRT. The prepared solution is for single patient use only. Aseptic technique should be used throughout administration to the patient. Discard any unused solution.

2.2 Dosing Considerations
PRISMASOL replacement solutions contain 4 different combinations of active ingredients (7 different products with varying ingredient amounts). PHOXILLUM replacement solutions contain 2 different combinations of active ingredients (2 different products with varying ingredient amounts). PRISMASOL and PHOXILLUM are supplied in a two-compartment bag that must be mixed immediately prior to use [see Dosage and Administration (2.3)]:

- Small compartment A (250 mL) containing an electrolyte solution, and
- Large compartment B (4750 mL) containing the buffer solution.

See Table 1for the concentrations of the active ingredients (after mixing) in these 9 different replacement solutions (total volume is 5 Liters).

The mode of therapy, solute formulation, flow rates, and length of PRISMASOL and PHOXILLUM replacement therapy in CRRT should be established by a physician based on the patient’s clinical condition, blood concentration of phosphate and other electrolytes, acid-base and glucose balance. Administer either PRISMASOL or PHOXILLUM into the extracorporeal circuit:

- Before (pre-dilution) the hemofilter or hemodiafilter,
- After (post-dilution) the hemofilter or hemodiafilter, or
- Before and after the hemofilter or hemodiafilter.

2.3 Preparing the Solution

Use only if the overwrap is not damaged, all seals are intact, peel seal is not broken, and the solution is clear. The solution may be warmed to 37°C/98.6°F prior to removing the overwrap to enhance patient comfort. However, only dry heat should be used. Solutions should not be heated in water or in a microwave oven. After heating, verify that the solution remains clear and contains no particulate matter.

The solutions are supplied in two different two-compartment bags made of polyolefin with a peel seal separating compartment A and B (see Figure 1).

Follow the instructions below when connecting the solution bags for correct use of the access ports.

2.4 Adding Drugs to the Solutions

After mixing, additional drugs may be added to the bag via injection connector (spike connector) in large compartment B. In general, administer drugs other than phosphate through a different access line.

When introducing drugs, use aseptic techniques and mix thoroughly prior to connecting the solution bag to the extracorporeal circuit.

Do not use if there is a color change and/or the appearance of precipitates, insoluble complexes or crystals after addition of medication.

Phosphate:Up to 1.2 mmol/L of phosphate can be added to the bag as potassium phosphate or sodium phosphate. The total potassium concentration of PRISMASOL solution should not exceed 4 mEq/L.
Use sodium phosphate to add phosphate if the total potassium concentration in PRISMASOL solution is 4 mEq/L.

PHOXILLUM Solutions:
Phosphate:Phosphate up to 0.2 mmol/L may be added to the solution. Use sodium phosphate if adding phosphate to bag. The total phosphate concentration should not exceed 1.2 mmol/L.

3 DOSAGE FORMS AND STRENGTHS
See Table 1for the concentrations of the active ingredients (after mixing) in these 9 different replacement solutions [see Dosage and Administration (2.2)].

4 CONTRAINDICATIONS
PHOXILLUM and PRISMASOL replacement solutions are contraindicated in patients with known hypersensitivities to these products.

5 WARNINGS AND PRECAUTIONS

5.1 Electrolyte and Volume Abnormalities
PHOXILLUM and PRISMASOL solutions can affect electrolytes and volume and may result in hyperkalemia or hyperphosphatemia. Monitor hemodynamic status and fluid inputs and outputs, potassium, phosphorous, calcium, other electrolytes and acid-base balance throughout the procedure. Abnormalities may be corrected by changing the formulation of replacement solution and/or dialysate, supplementation, or adjusting flow rates appropriately [see Dosage and Administration (2)].

PHOXILLUM replacement solutions contain hydrogen phosphate, a weak acid that may increase the risk of metabolic acidosis.

5.2 Blood Glucose Abnormalities
The use of PRISMASOL and PHOXILLUM replacement solutions can affect blood glucose levels resulting in hypo- or hyper-glycemia depending upon the dextrose content of the replacement solution. Monitor blood glucose levels regularly. Patients may require initiation of or modification of antidiabetic therapy or othercorrective measures during treatment.

6 ADVERSE REACTIONS
The following adverse reactions have been identified during postapproval use with these or other similar products and therefore may occur with use of PHOXILLUM or PRISMASOL. Because these reactions are reported voluntarily from a population of uncertain size, it is not always possible to reliably estimate their frequency or establish a causal relationship to drug exposure.

- Metabolic acidosis
- Hypotension
- Acid-base disorders
- Electrolyte imbalance including calcium ionized increased (reported in PRISMASOL solutions containing calcium), hyperphosphatemia, and hypophosphatemia
- Fluid imbalance

7 DRUG INTERACTIONS
As with the use of other replacement solutions, blood concentrations of dialyzable drugs may be reduced by CRRT due to their removal by the hemofilter or hemodiafilter. The blood concentrations of certain drugs may need to be monitored and appropriate therapy implemented to correct for removal during treatment.

7.1 Citrate
When used as an anticoagulant, citrate contributes to the overall buffer load and can reduce plasma calcium levels. Select the PRISMASOL/PHOXILLUM formulation(s) accordingly.

8 USE IN SPECIFIC POPULATIONS
8.1 Pregnancy
Risk Summary
PRISMASOL and PHOXILLUM are pharmacologically inactive solutions. While there are no adequate and well controlled studies in pregnant women, appropriate administration of PRISMASOL and PHOXILLUM solutions with monitoring of fluid, electrolyte, acid-base and glucose balance, is not expected to cause fetal harm. Animal reproduction studies have not been conducted with PRISMASOL and PHOXILLUM solutions.

The estimated background risk of major birth defects and miscarriage for the indicated population are unknown. All pregnancies have a background risk of birth defect, loss or other adverse outcomes. In the U.S. general population, the estimated background risk of major birth defects and miscarriage in clinically recognized pregnancies is 2 to 4% and 15 to 20%, respectively.

Clinical Considerations
Maintenance of normal acid-base balance is important for fetal well-being.

8.2 Lactation
Risk Summary
The components of PRISMASOL and PHOXILLUM solutions are excreted in human milk. Appropriate administration of PRISMASOL and PHOXILLUM solutions with monitoring of fluid, electrolyte, acid-base and glucose balance, is not expected to harm a nursing infant.

8.4 Pediatric Use
Safety and effectiveness have been established based on published clinical data of CRRT replacement solutions with compositions similar to PRISMASOL and PHOXILLUM used in adults and two hemofiltration studies in pediatric patients, including a study of newborns to 17 years old.

8.5 Geriatric Use
The experience with PRISMASOL and PHOXILLUM solutions in geriatric patients has not identified novel concerns.

11 DESCRIPTION
PRISMASOL and PHOXILLUM solutions are clear, sterile, free of bacterial endotoxins and contain no bacteriostatic or antimicrobial agents. These solutions are used in Continuous Renal Replacement Therapies (CRRT) as a replacement solution in hemofiltration and hemodiafiltration. Depending on the product (see Table 2), the two compartments contain:

Calcium chloride, USP, is chemically designated calcium chloride dihydrate (CaCl2• 2H2O).
Magnesium chloride, USP, is chemically designated magnesium chloride hexahydrate (MgCl2• 6H2O).
Sodium chloride, USP, is chemically designated NaCl.
Potassium chloride, USP, is chemically designated KCl.
Sodium bicarbonate, USP, is chemically designated NaHCO3.
Dextrose, USP, is chemically designated D-Glucose anhydrous (C6H12O6) or D-Glucose monohydrate (C6H12O6 • H2O).
Lactic acid, USP, is chemically designated CH3CH(OH)COOH.
Dibasic sodium phosphate, USP, is chemically designated as disodium hydrogen phosphate, dihydrate (Na2HPO4• 2H2O)

The pH of the final solution is in the range of 7.0 to 8.5.

12 CLINICAL PHARMACOLOGY
12.1 Mechanism of Action
PRISMASOL and PHOXILLUM solutions are pharmacologically inactive. The electrolyte concentrations in the solutions are chosen to restore plasma levels to clinically desired concentrations or maintain plasma levels at the desired concentrations.

PRISMASOL and PHOXILLUM solutions are used as replacement solution to replace water and electrolytes removed during hemofiltration and hemodiafiltration. Bicarbonate (or precursor lactate) in the solution is used as an alkalinizing buffer to restore acid-base balance to a clinically desirable level.

12.3 Pharmacokinetics
The distribution of electrolytes, bicarbonate, and dextrose is determined by the patient’s clinical condition, metabolic status, and residual renal function. The elimination and replacement of water, electrolytes and buffer depend on the patient’s electrolyte and acid-base balance, metabolic status, residual renal function and ongoing physiologic losses through intestinal, respiratory and cutaneous routes.

16 HOW SUPPLIED/STORAGE AND HANDLING
PRISMASOL and PHOXILLUM solutions are supplied in a two-compartment bag made of polyolefin. The 5000 mL bag is composed of a small compartment (250 mL) and a large compartment (4750 mL). The two compartments are separated by a peel seal.

The bag is overwrapped with a transparent overwrap. See Table 2for the concentrations of the active ingredients in each compartment for each product [see Description (11)].

Container | Fill Volume | NDC
PRISMASOL Solutions
PRISMASOL BGK0/2.5 | 5000 mL | 24571-108-06
PRISMASOL BGK4/2.5 | 5000 mL | 24571-105-06
PRISMASOL BGK2/3.5 | 5000 mL | 24571-103-06
PRISMASOL BGK2/0 | 5000 mL | 24571-102-06
PRISMASOL B22GK4/0 | 5000 mL | 24571-111-06
PRISMASOL BK0/0/1.2 | 5000 mL | 24571-113-06
PRISMASOL BGK4/0/1.2 | 5000 mL | 24571-114-06
PHOXILLUM Solutions
PHOXILLUM BK4/2.5 | 5000 mL | 24571-116-06
PHOXILLUM B22K4/0 | 5000 mL | 24571-117-06

Not all formulations may be marketed.

Storage conditions
Store at 20°C to 25°C (68°F to 77°F); excursions permitted to 15ºC to 30ºC (59ºF to 86ºF). [See USP
Controlled Room Temperature]

Do not freeze or expose to excessive heat. Do not use if precipitate has formed or if container seals have
been damaged.

Manufactured for:
Vantive US Healthcare LLC
One Baxter Parkway
Deerfield, Illinois 60015

07-19-00-6103